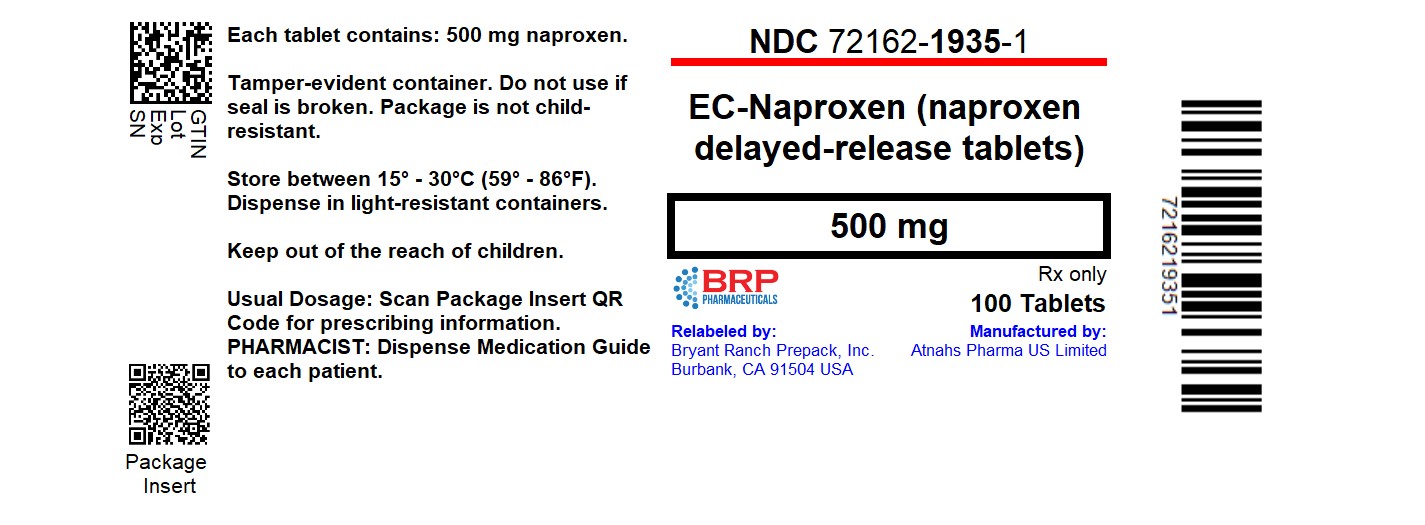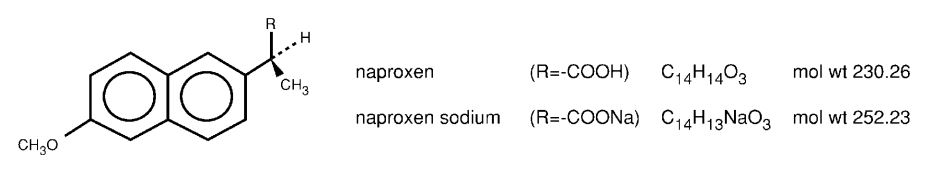 DRUG LABEL: EC-NAPROXEN
NDC: 72162-1935 | Form: TABLET, DELAYED RELEASE
Manufacturer: Bryant Ranch Prepack
Category: prescription | Type: HUMAN PRESCRIPTION DRUG LABEL
Date: 20250306

ACTIVE INGREDIENTS: NAPROXEN 500 mg/1 1
INACTIVE INGREDIENTS: CROSCARMELLOSE SODIUM; POVIDONE K90; MAGNESIUM STEARATE; METHACRYLIC ACID - METHYL METHACRYLATE COPOLYMER (1:1); TALC; TRIETHYL CITRATE; SODIUM HYDROXIDE; WATER

HIGHLIGHTS OF PRESCRIBING INFORMATION

These highlights do not include all the information needed to use NAPROXEN Tablets, EC-NAPROXEN and NAPROXEN SODIUM safely and effectively. See full prescribing information for NAPROXEN, EC-NAPROXEN and NAPROXEN SODIUM.
NAPROXEN (naproxen) tablets,
EC-NAPROXEN (naproxen delayed-release tablets),
NAPROXEN SODIUM (naproxen sodium tablets), for oral use
Initial U.S. Approval: 1976

RECENT MAJOR CHANGES

Warnings and Precautions (5.10, 5.11) 04/2021

WARNING: RISK OF SERIOUS CARDIOVASCULAR AND GASTROINTESTINAL EVENTS

See full prescribing information for complete boxed warning.

- Nonsteroidal anti-inflammatory drugs (NSAIDs) cause an increased risk of serious cardiovascular thrombotic events, including myocardial infarction and stroke, which can be fatal. This risk may occur early in treatment and may increase with duration of use. (5.1)

- NAPROXEN Tablets, EC-NAPROXEN and NAPROXEN SODIUM are contraindicated in the setting of coronary artery bypass graft (CABG) surgery. (4, 5.1)

- NSAIDs cause an increased risk of serious gastrointestinal (GI) adverse events including bleeding, ulceration, and perforation of the stomach or intestines, which can be fatal. These events can occur at any time during use and without warning symptoms. Elderly patients and patients with a prior history of peptic ulcer disease and/or GI bleeding are at greater risk for serious GI events.(5.2)

1 INDICATIONS AND USAGE

NAPROXEN Tablets, EC-NAPROXEN, and NAPROXEN SODIUM are non-steroidal anti-inflammatory drugs indicated for:

the relief of the signs and symptoms of:

- rheumatoid arthritis
- osteoarthritis
- ankylosing spondylitis
- polyarticular juvenile idiopathic arthritis

NAPROXEN Tablets and NAPROXEN SODIUM are also indicated for:

the relief of signs and symptoms of:

- tendonitis
- bursitis
- acute gout

the management of:

- pain
- primary dysmenorrhea

2 DOSAGE AND ADMINISTRATION

Use the lowest effective dosage for shortest duration consistent with individual patient treatment goals. (2.1)

Rheumatoid Arthritis, Osteoarthritis, and Ankylosing Spondylitis

NAPROXEN Tablets | 250 mg (one-half tablet) 500 mg | twice daily
NAPROXEN SODIUM | 275 mg (one-half tablet) 550 mg | twice daily
EC-NAPROXEN | 375 mg or 500 mg | twice daily

To maintain the integrity of the enteric coating, the EC-NAPROXEN tablet should not be broken, crushed or chewed during ingestion.

The dose may be adjusted up or down depending on the clinical response of the patient. In patients who tolerate lower doses well, the dose may be increased to naproxen 1,500 mg/day for up to 6 months.

Polyarticular Juvenile Idiopathic Arthritis

NAPROXEN Tablets may not allow for the flexible dose titration needed in pediatric patients with polyarticular juvenile idiopathic arthritis. A liquid formulation may be more appropriate.

Recommended total daily dose of naproxen is approximately 10 mg/kg given in 2 divided doses. Dosing with NAPROXEN Tablets is not appropriate for children weighing less than 50 kilograms.

Management of Pain, Primary Dysmenorrhea, and Acute Tendonitis and Bursitis

Recommended starting dose 550 mg of naproxen sodium as NAPROXEN SODIUM followed by 550 mg every 12 hours or 275 mg every 6 to 8 hours as required. The initial total daily dose should not exceed 1375 mg of naproxen sodium. Thereafter, the total daily dose should not exceed 1100 mg of naproxen sodium. NAPROXEN SODIUM is recommended for the management of acute painful conditions when prompt onset of pain relief is desired.

Acute Gout

Recommended starting dose 750 mg of NAPROXEN Tablets followed by 250 mg every 8 hours until the attack has subsided. NAPROXEN SODIUM may also be used at a starting dose of 825 mg followed by 275 mg every 8 hours. EC-NAPROXEN is not recommended because of the delay in absorption.

3 DOSAGE FORMS AND STRENGTHS

NAPROXEN® (naproxen) tablets: 500 mg
EC-NAPROXEN® (naproxen) delayed-release tablets: 375 mg and 500 mg
NAPROXEN SODIUM (naproxen sodium) tablets: 550 mg (contains 50 mg of sodium)

4 CONTRAINDICATIONS

- Known hypersensitivity to naproxen or any components of the drug product (4)
- History of asthma, urticaria, or other allergic-type reactions after taking aspirin or other NSAIDs (4)
- In the setting of CABG surgery (4)

5 WARNINGS AND PRECAUTIONS

Hepatotoxicity: Inform patients of warning signs and symptoms of hepatotoxicity. Discontinue if abnormal liver tests persist or worsen or if clinical signs and symptoms of liver disease develop. (5.3)

Hypertension:Patients taking some antihypertensive medications may have impaired response to these therapies when taking NSAIDs. Monitor blood pressure. (5.4, 7)

Heart Failure and Edema:Avoid use of NAPROXEN Tablets, EC-NAPROXEN and NAPROXEN SODIUM in patients with severe heart failure unless benefits are expected to outweigh risk of worsening heart failure. (5.5)

Renal Toxicity:Monitor renal function in patients with renal or hepatic impairment, heart failure, dehydration, or hypovolemia. Avoid use of NAPROXEN Tablets, EC-NAPROXEN and NAPROXEN SODIUM in patients with advanced renal disease unless benefits are expected to outweigh risk of worsening renal function. (5.6)

Anaphylactic Reactions:Seek emergency help if an anaphylactic reaction occurs. (5.7)

Exacerbation of Asthma Related to Aspirin Sensitivity:NAPROXEN Tablets, EC-NAPROXEN and NAPROXEN SODIUM are contraindicated in patients with aspirin-sensitive asthma. Monitor patients with preexisting asthma (without aspirin sensitivity). (5.8)

Serious Skin Reactions:Discontinue NAPROXEN Tablets, EC-NAPROXEN and NAPROXEN SODIUM at first appearance of skin rash or other signs of hypersensitivity. (5.9)

Drug Reaction with Eosinophilia and Systemic Symptoms (DRESS):Discontinue and evaluate clinically (5.10).

Fetal Toxicity:Limit use of NSAIDs, including NAPROXEN Tablets, EC-NAPROXEN, and NAPROXEN SODIUM, between about 20 to 30 weeks in pregnancy due to the risk of oligohydramnios/fetal dysfunction. Avoid use of NSAIDs in women at about 30 weeks gestation and later in pregnancy due to the risks of oligohydramnios/fetal renal dysfunction and premature closure of the fetal ductus arteriosus. (5.11, 8.1)

Hematologic Toxicity:Monitor hemoglobin or hematocrit in patients with any signs or symptoms of anemia. (5.12, 7)

6 ADVERSE REACTIONS

Most common adverse reactions to naproxen were dyspepsia, abdominal pain, nausea, headache, rash, ecchymosis, and edema. (6.1)

To report SUSPECTED ADVERSE REACTIONS, contact Woodward Pharma Services LLC at 1-888-514-4727 or FDA at 1-800-FDA-1088 or www.fda.gov/medwatch.

7 DRUG INTERACTIONS

Drugs that Interfere with Hemostasis (e.g. warfarin, aspirin, SSRIs/SNRIs):

Monitor patients for bleeding who are concomitantly taking NAPROXEN Tablets, EC-NAPROXEN or NAPROXEN SODIUM with drugs that interfere with hemostasis. Concomitant use of NAPROXEN Tablets, EC-NAPROXEN or NAPROXEN SODIUM and analgesic doses of aspirin is not generally recommended. (7)

ACE inhibitors, Angiotensin Receptor Blockers (ARB), or Beta-Blockers:Concomitant use with NAPROXEN Tablets, EC-NAPROXEN or NAPROXEN SODIUM may diminish the antihypertensive effect of these drugs. Monitor blood pressure. (7)

ACE Inhibitors and ARBs:Concomitant use with NAPROXEN Tablets, EC-NAPROXEN or NAPROXEN SODIUM in elderly, volume depleted, or those with renal impairment may result in deterioration of renal function. In such high risk patients, monitor for signs of worsening renal function. (7)

Diuretics:NSAIDs can reduce natriuretic effect of furosemide and thiazide diuretics. Monitor patients to assure diuretic efficacy including antihypertensive effects. (7)

Digoxin:Concomitant use with NAPROXEN Tablets, EC-NAPROXEN or NAPROXEN SODIUM can increase serum concentration and prolong half-life of digoxin. Monitor serum digoxin levels. (7)

8 USE IN SPECIFIC POPULATIONS

Infertility:NSAIDs are associated with reversible infertility. Consider withdrawal of NAPROXEN Tablets, EC-NAPROXEN and NAPROXEN SODIUM in women who have difficulties conceiving. (8.3)

Renal Impairment:Naproxen-containing products are not recommended for use in patients with moderate to severe and severe renal impairment (creatinine clearance <30 mL/min). (8.7)

FULL PRESCRIBING INFORMATION

WARNING: RISK OF SERIOUS CARDIOVASCULAR AND GASTROINTESTINAL EVENTS

Cardiovascular Thrombotic Events

- Nonsteroidal anti-inflammatory drugs (NSAIDs) cause an increased risk of serious cardiovascular thrombotic events, including myocardial infarction and stroke, which can be fatal. This risk may occur early in treatment and may increase with duration of use [ see Warnings and Precautions (5.1)].
- Naproxen tablets are contraindicated in the setting of coronary artery bypass graft (CABG) surgery [ see Contraindications (4), Warnings and Precautions (5.1)].

Gastrointestinal Bleeding, Ulceration, and Perforation

- NSAIDs cause an increased risk of serious gastrointestinal (GI) adverse events including bleeding, ulceration, and perforation of the stomach or intestines, which can be fatal. These events can occur at any time during use and without warning symptoms. Elderly patients and patients with a prior history of peptic ulcer disease and/or GI bleeding are at greater risk for serious GI events [ see Warnings and Precautions (5.2)].

1 INDICATIONS AND USAGE

NAPROXEN Tablets, EC-NAPROXEN, and NAPROXEN SODIUM are indicated for:

the relief of the signs and symptoms of:

- rheumatoid arthritis
- osteoarthritis
- ankylosing spondylitis
- polyarticular juvenile idiopathic arthritis

NAPROXEN Tablets and NAPROXEN SODIUM are also indicated for:

the relief of signs and symptoms of:

- tendonitis
- bursitis
- acute gout

the management of:

- pain
- primary dysmenorrhea

2 DOSAGE AND ADMINISTRATION

2.1 General Dosing Instructions

Carefully consider the potential benefits and risks of NAPROXEN Tablets, EC-NAPROXEN and NAPROXEN SODIUM and other treatment options before deciding to use NAPROXEN Tablets, EC-NAPROXEN and NAPROXEN SODIUM. Use the lowest effective dose for the shortest duration consistent with individual patient treatment goals [see Warnings and Precautions (5)] .

After observing the response to initial therapy with NAPROXEN Tablets, EC-NAPROXEN or NAPROXEN SODIUM, the dose and frequency should be adjusted to suit an individual patient's needs.

To maintain the integrity of the enteric coating, the EC-NAPROXEN tablet should not be broken, crushed or chewed during ingestion.

Naproxen-containing products such as NAPROXEN, EC-NAPROXEN and NAPROXEN SODIUM, and other naproxen products should not be used concomitantly since they all circulate in the plasma as the naproxen anion.

2.2 Rheumatoid Arthritis, Osteoarthritis and Ankylosing Spondylitis

The recommended dosages of NAPROXEN Tablets, NAPROXEN SODIUM, and EC-NAPROXEN are shown in Table 1.

Table 1: Recommended dosages for NAPROXEN Tablets, NAPROXEN SODIUM, and EC-NAPROXEN
NAPROXEN Tablets | 250 mg (one-half tablet) 500 mg | twice daily
NAPROXEN SODIUM | 275 mg (one-half tablet) 550 mg (naproxen 500 mg with 50 mg sodium) | twice daily
EC- NAPROXEN | 375 mg or 500 mg | twice daily

During long-term administration, the dose of naproxen may be adjusted up or down depending on the clinical response of the patient. A lower daily dose may suffice for long-term administration.

The morning and evening doses do not have to be equal in size and administration of the drug more frequently than twice daily does not generally make a difference in response.

In patients who tolerate lower doses well, the dose may be increased to naproxen 1500 mg/day for limited periods of up to 6 months when a higher level of anti-inflammatory/analgesic activity is required. When treating such patients with naproxen 1500 mg/day, the physician should observe sufficient increased clinical benefits to offset the potential increased risk.

2.3 Polyarticular Juvenile Idiopathic Arthritis

Naproxen solid-oral dosage forms may not allow for the flexible dose titration needed in pediatric patients with polyarticular juvenile idiopathic arthritis. A liquid formulation may be more appropriate for weight-based dosing and due to the need for dose flexibility in children.

In pediatric patients, doses of 5 mg/kg/day produced plasma levels of naproxen similar to those seen in adults taking 500 mg of naproxen [see Clinical Pharmacology (12)] . The recommended total daily dose of naproxen is approximately 10 mg/kg given in 2 divided doses. Dosing with NAPROXEN tablets is not appropriate for children weighing less than 50 kilograms.

2.4 Management of Pain, Primary Dysmenorrhea, and Acute Tendonitis and Bursitis

The recommended starting dose of NAPROXEN SODIUM (naproxen sodium) tablets is 550 mg followed by 550 mg every 12 hours or 275 mg (one half of a 550 mg tablet) every 6 to 8 hours as required. The initial total daily dose should not exceed 1375 mg (two and one-half tablets) of naproxen sodium. Thereafter, the total daily dose should not exceed 1100 mg of naproxen sodium. Because the sodium salt of naproxen is more rapidly absorbed, NAPROXEN SODIUM is recommended for the management of acute painful conditions when prompt onset of pain relief is desired. NAPROXEN Tablets may also be used. The recommended starting dose of NAPROXEN Tablets is 500 mg followed by 250 mg (one half of a 500 mg NAPROXEN tablet) every 6-8 hours as required.. The total daily dose should not exceed 1250 mg of naproxen.

EC-NAPROXEN is not recommended for initial treatment of acute pain because absorption of naproxen is delayed compared to other naproxen-containing products [see Clinical Pharmacology (12)] .

2.5 Acute Gout

The recommended starting dose is 750 mg (one and one-half tablets) of NAPROXEN Tablets followed by 250 mg (one-half tablet) every 8 hours until the attack has subsided. NAPROXEN SODIUM may also be used at a starting dose of 825 mg (one and one-half tablets) followed by 275 mg (one-half tablet) every 8 hours. EC-NAPROXEN is not recommended because of the delay in absorption.

2.6 Non-Interchangeability with Other Formulations of Naproxen

Different dose strengths and formulations (e.g., tablets, suspension) of naproxen are not interchangeable. This difference should be taken into consideration when changing strengths or formulations.

3 DOSAGE FORMS AND STRENGTHS

NAPROXEN (naproxen) tablets: 500 mg: yellow, capsule-shaped, engraved with NPR LE 500 on one side and scored on the other.

EC-NAPROXEN (naproxen) delayed-release tablets: 375 mg: white, oval biconvex coated tablets imprinted with NPR EC 375 on one side.

EC-NAPROXEN (naproxen) delayed-release tablets: 500 mg: white, oblong coated tablets imprinted with NPR EC 500 on one side.

NAPROXEN SODIUM (naproxen sodium) tablets: 550 mg: dark blue, oblong-shaped, engraved with NPS 550 on one side and scored on both sides.

4 CONTRAINDICATIONS

NAPROXEN Tablets, EC-NAPROXEN, and NAPROXEN SODIUM are contraindicated in the following patients:

- Known hypersensitivity (e.g., anaphylactic reactions and serious skin reactions) to naproxen or any components of the drug product [see Warnings and Precautions (5.7, 5.9)].
- History of asthma, urticaria, or other allergic-type reactions after taking aspirin or other NSAIDs. Severe, sometimes fatal, anaphylactic reactions to NSAIDs have been reported in such patients [see Warnings and Precautions (5.7, 5.8)] .
- In the setting of coronary artery bypass graft (CABG) surgery [see Warnings and Precautions (5.1)] .

5 WARNINGS AND PRECAUTIONS

5.1 Cardiovascular Thrombotic Events

Clinical trials of several COX-2 selective and nonselective NSAIDs of up to three years duration have shown an increased risk of serious cardiovascular (CV) thrombotic events, including myocardial infarction (MI) and stroke, which can be fatal. Based on available data, it is unclear that the risk for CV thrombotic events is similar for all NSAIDs. The relative increase in serious CV thrombotic events over baseline conferred by NSAID use appears to be similar in those with and without known CV disease or risk factors for CV disease. However, patients with known CV disease or risk factors had a higher absolute incidence of excess serious CV thrombotic events, due to their increased baseline rate. Some observational studies found that this increased risk of serious CV thrombotic events began as early as the first weeks of treatment. The increase in CV thrombotic risk has been observed most consistently at higher doses.

To minimize the potential risk for an adverse CV event in NSAID-treated patients, use the lowest effective dose for the shortest duration possible. Physicians and patients should remain alert for the development of such events, throughout the entire treatment course, even in the absence of previous CV symptoms. Patients should be informed about the symptoms of serious CV events and the steps to take if they occur.

There is no consistent evidence that concurrent use of aspirin mitigates the increased risk of serious CV thrombotic events associated with NSAID use. The concurrent use of aspirin and an NSAID, such as naproxen, increases the risk of serious gastrointestinal (GI) events [see Warnings and Precautions (5.2)] .

Status Post Coronary Artery Bypass Graft (CABG) Surgery

Two large, controlled, clinical trials of a COX-2 selective NSAID for the treatment of pain in the first 10 to 14 days following CABG surgery found an increased incidence of myocardial infarction and stroke. NSAIDs are contraindicated in the setting of CABG [see Contraindications (4)] .

Post-MI Patients

Observational studies conducted in the Danish National Registry have demonstrated that patients treated with NSAIDs in the post-MI period were at increased risk of reinfarction, CV-related death, and all-cause mortality beginning in the first week of treatment. In this same cohort, the incidence of death in the first year post-MI was 20 per 100 person years in NSAID-treated patients compared to 12 per 100 person years in non-NSAID exposed patients. Although the absolute rate of death declined somewhat after the first year post-MI, the increased relative risk of death in NSAID users persisted over at least the next four years of follow-up.

Avoid the use of NAPROXEN Tablets, EC-NAPROXEN, and NAPROXEN SODIUM in patients with a recent MI unless the benefits are expected to outweigh the risk of recurrent CV thrombotic events. If NAPROXEN Tablets, EC-NAPROXEN and NAPROXEN SODIUM are used in patients with a recent MI, monitor patients for signs of cardiac ischemia.

5.2 Gastrointestinal Bleeding, Ulceration, and Perforation

NSAIDs, including naproxen cause serious gastrointestinal (GI) adverse events including inflammation, bleeding, ulceration, and perforation of the esophagus, stomach, small intestine, or large intestine, which can be fatal. These serious adverse events can occur at any time, with or without warning symptoms, in patients treated with NSAIDs.

Only one in five patients who develop a serious upper GI adverse event on NSAID therapy, is symptomatic. Upper GI ulcers, gross bleeding, or perforation caused by NSAIDs occured in approximately 1% of patients treated for 3-6 months, and in about 2%-4% of patients treated for one year. However, even short-term NSAID therapy is not without risk.

Risk Factors for GI Bleeding, Ulceration, and Perforation

Patients with a prior history of peptic ulcer disease and/or GI bleeding who used NSAIDs had a greater than 10-fold increased risk for developing a GI bleed compared to patients without these risk factors. Other factors that increase the risk of GI bleeding in patients treated with NSAIDs include longer duration of NSAID therapy; concomitant use of oral corticosteroids, aspirin, anticoagulants, or selective serotonin reuptake inhibitors (SSRIs); smoking; use of alcohol; older age; and poor general health status. Most postmarketing reports of fatal GI events occurred in elderly or debilitated patients. Additionally, patients with advanced liver disease and/or coagulopathy are at increased risk for GI bleeding.

Strategies to Minimize the GI Risks in NSAID-treated patients:

- Use the lowest effective dosage for the shortest possible duration.
- Avoid administration of more than one NSAID at a time.
- Avoid use in patients at higher risk unless benefits are expected to outweigh the increased risk of bleeding. For such patients, as well as those with active GI bleeding, consider alternate therapies other than NSAIDs.
- Remain alert for signs and symptoms of GI ulceration and bleeding during NSAID therapy.
- If a serious GI adverse event is suspected, promptly initiate evaluation and treatment, and discontinue NAPROXEN Tablets, EC-NAPROXEN, or NAPROXEN SODIUM until a serious GI adverse event is ruled out.
- In the setting of concomitant use of low-dose aspirin for cardiac prophylaxis, monitor patients more closely for evidence of GI bleeding [see Drug Interactions (7)] .

5.3 Hepatotoxicity

Elevations of ALT or AST (three or more times the upper limit of normal [ULN]) have been reported in approximately 1% of NSAID-treated patients in clinical trials. In addition, rare, sometimes fatal, cases of severe hepatic injury, including fulminant hepatitis, liver necrosis and hepatic failure have been reported.

Elevations of ALT or AST (less than three times ULN) may occur in up to 15% of patients treated with NSAIDs including naproxen.

Inform patients of the warning signs and symptoms of hepatotoxicity (e.g., nausea, fatigue, lethargy, diarrhea, pruritus, jaundice, right upper quadrant tenderness, and "flu-like" symptoms). If clinical signs and symptoms consistent with liver disease develop, or if systemic manifestations occur (e.g., eosinophilia, rash, etc.), discontinue NAPROXEN Tablets, EC-NAPROXEN, or NAPROXEN SODIUM immediately, and perform a clinical evaluation of the patient.

5.4 Hypertension

NSAIDs, including NAPROXEN Tablets, EC-NAPROXEN, and NAPROXEN SODIUM, can lead to new onset of hypertension or worsening of pre-existing hypertension, either of which may contribute to the increased incidence of CV events. Patients taking angiotensin converting enzyme (ACE) inhibitors, thiazide diuretics, or loop diuretics may have impaired response to these therapies when taking NSAIDs [see Drug Interactions (7)] .

Monitor blood pressure (BP) during the initiation of NSAID treatment and throughout the course of therapy.

5.5 Heart Failure and Edema

The Coxib and traditional NSAID Trialists' Collaboration meta-analysis of randomized controlled trials demonstrated an approximately two-fold increase in hospitalization for heart failure in COX-2 selective-treated patients and nonselective NSAID-treated patients compared to placebo-treated patients. In a Danish National Registry study of patients with heart failure, NSAID use increased the risk of MI, hospitalization for heart failure, and death.

Additionally, fluid retention and edema have been observed in some patients treated with NSAIDs. Use of naproxen may blunt the CV effects of several therapeutic agents used to treat these medical conditions (e.g., diuretics, ACE inhibitors, or angiotensin receptor blockers [ARBs]) [see Drug Interactions (7)] .

Avoid the use of NAPROXEN Tablets, EC-NAPROXEN, or NAPROXEN SODIUM in patients with severe heart failure unless the benefits are expected to outweigh the risk of worsening heart failure. If NAPROXEN Tablets, EC-NAPROXEN, or NAPROXEN SODIUM is used in patients with severe heart failure, monitor patients for signs of worsening heart failure.

Since each NAPROXEN SODIUM tablet contains 50 mg of sodium (about 2 mEq per each 500 mg of naproxen), this should be considered in patients whose overall intake of sodium must be severely restricted.

5.6 Renal Toxicity and Hyperkalemia

Renal Toxicity

Long-term administration of NSAIDs has resulted in renal papillary necrosis and other renal injury.

Renal toxicity has also been seen in patients in whom renal prostaglandins have a compensatory role in the maintenance of renal perfusion. In these patients, administration of an NSAID may cause a dose-dependent reduction in prostaglandin formation and, secondarily, in renal blood flow, which may precipitate overt renal decompensation. Patients at greatest risk of this reaction are those with impaired renal function, dehydration, hypovolemia, heart failure, liver dysfunction, those taking diuretics and ACE inhibitors or ARBs, and the elderly. Discontinuation of NSAID therapy is usually followed by recovery to the pretreatment state.

No information is available from controlled clinical studies regarding the use of NAPROXEN Tablets, EC-NAPROXEN, or NAPROXEN SODIUM in patients with advanced renal disease. The renal effects of NAPROXEN Tablets, EC-NAPROXEN, or NAPROXEN SODIUM may hasten the progression of renal dysfunction in patients with preexisting renal disease.

Correct volume status in dehydrated or hypovolemic patients prior to initiating NAPROXEN Tablets, EC-NAPROXEN, or NAPROXEN SODIUM. Monitor renal function in patients with renal or hepatic impairment, heart failure, dehydration, or hypovolemia during use of NAPROXEN Tablets, EC-NAPROXEN, and NAPROXEN SODIUM [ see Drug Interactions (7)]. Avoid the use of NAPROXEN Tablets, EC-NAPROXEN, and NAPROXEN SODIUM in patients with advanced renal disease unless the benefits are expected to outweigh the risk of worsening renal function. If NAPROXEN Tablets, EC-NAPROXEN, or NAPROXEN SODIUM is used in patients with advanced renal disease, monitor patients for signs of worsening renal function.

Hyperkalemia

Increases in serum potassium concentration, including hyperkalemia, have been reported with use of NSAIDs, even in some patients without renal impairment. In patients with normal renal function, these effects have been attributed to a hyporeninemic-hypoaldosteronism state.

5.7 Anaphylactic Reactions

Naproxen has been associated with anaphylactic reactions in patients with and without known hypersensitivity to naproxen and in patients with aspirin-sensitive asthma [ see Contraindications (4)and Warnings and Precautions (5.8)].

Seek emergency help if an anaphylactic reaction occurs.

5.8 Exacerbation of Asthma Related to Aspirin Sensitivity

A subpopulation of patients with asthma may have aspirin-sensitive asthma which may include chronic rhinosinusitis complicated by nasal polyps; severe, potentially fatal bronchospasm; and/or intolerance to aspirin and other NSAIDs. Because cross-reactivity between aspirin and other NSAIDs has been reported in such aspirin-sensitive patients, NAPROXEN Tablets, EC-NAPROXEN, and NAPROXEN SODIUM are contraindicated in patients with this form of aspirin sensitivity [ see Contraindications (4)]. When NAPROXEN Tablets, EC-NAPROXEN, or NAPROXEN SODIUM is used in patients with preexisting asthma (without known aspirin sensitivity), monitor patients for changes in the signs and symptoms of asthma.

5.9 Serious Skin Reactions

NSAIDs, including naproxen, can cause serious skin adverse reactions such as exfoliative dermatitis, Stevens-Johnson Syndrome (SJS), and toxic epidermal necrolysis (TEN), which can be fatal. These serious events may occur without warning. Inform patients about the signs and symptoms of serious skin reactions, and to discontinue the use of NAPROXEN Tablets, EC-NAPROXEN, or NAPROXEN SODIUM at the first appearance of skin rash or any other sign of hypersensitivity. NAPROXEN Tablets, EC-NAPROXEN, and NAPROXEN SODIUM are contraindicated in patients with previous serious skin reactions to NSAIDs [ see Contraindications (4)].

5.10 Drug Reaction with Eosinophilia and Systemic Symptoms (DRESS)

Drug Reaction with Eosinophilia and Systemic Symptoms (DRESS) has been reported in patients taking NSAIDs such as NAPROXEN Tablets, EC-NAPROXEN, and NAPROXEN SODIUM. Some of these events have been fatal or life-threatening. DRESS typically, although not exclusively, presents with fever, rash, lymphadenopathy, and/or facial swelling. Other clinical manifestations may include hepatitis, nephritis, hematological abnormalities, myocarditis, or myositis. Sometimes symptoms of DRESS may resemble an acute viral infection. Eosinophilia is often present. Because this disorder is variable in its presentation, other organ systems not noted here may be involved. It is important to note that early manifestations of hypersensitivity, such as fever or lymphadenopathy, may be present even though rash is not evident. If such signs or symptoms are present, discontinue NAPROXEN Tablets, EC-NAPROXEN, and NAPROXEN SODIUM and evaluate the patient immediately.

5.11 Fetal Toxicity

Premature Closure of Fetal Ductus Arteriosus:

Avoid use of NSAIDs, including NAPROXEN Tablets, EC-NAPROXEN, and NAPROXEN SODIUM, in pregnant women at about 30 weeks of gestation and later. NSAIDs, including NAPROXEN Tablets, EC-NAPROXEN, and NAPROXEN SODIUM, increase the risk of premature closure of the fetal ductus arteriosus at approximately this gestational age.

Oligohydramnios/Neonatal Renal Impairment:

Use of NSAIDs, including NAPROXEN Tablets, EC-NAPROXEN, and NAPROXEN SODIUM, at about 20 weeks gestation or later in pregnancy may cause fetal renal dysfunction leading to oligohydramnios and, in some cases, neonatal renal impairment. These adverse outcomes are seen, on average, after days to weeks of treatment, although oligohydramnios has been infrequently reported as soon as 48 hours after NSAID initiation. Oligohydramnios is often, but not always, reversible with treatment discontinuation. Complications of prolonged oligohydramnios may, for example, include limb contractures and delayed lung maturation. In some postmarketing cases of impaired neonatal renal function, invasive procedures such as exchange transfusion or dialysis were required.

If NSAID treatment is necessary between about 20 weeks and 30 weeks gestation, limit NAPROXEN Tablets, EC-NAPROXEN, or NAPROXEN SODIUM use to the lowest effective dose and shortest duration possible. Consider ultrasound monitoring of amniotic fluid if NAPROXEN Tablets, EC-NAPROXEN, or NAPROXEN SODIUM treatment extends beyond 48 hours. Discontinue NAPROXEN Tablets, EC-NAPROXEN, and NAPROXEN SODIUM if oligohydramnios occurs and follow up according to clinical practice [see Use in Specific Populations (8.1)]

5.12 Hematologic Toxicity

Anemia has occurred in NSAID-treated patients. This may be due to occult or gross blood loss, fluid retention, or an incompletely described effect on erythropoiesis. If a patient treated with NAPROXEN Tablets, EC-NAPROXEN, or NAPROXEN SODIUM has any signs or symptoms of anemia, monitor hemoglobin or hematocrit.

NSAIDs, including NAPROXEN Tablets, EC-NAPROXEN, and NAPROXEN SODIUM, may increase the risk of bleeding events. Co-morbid conditions such as coagulation disorders or concomitant use of warfarin and other anticoagulants, antiplatelet agents (e.g., aspirin), serotonin reuptake inhibitors (SSRIs), and serotonin norepinephrine reuptake inhibitors (SNRIs) may increase this risk. Monitor these patients for signs of bleeding [ see Drug Interactions (7)].

5.13 Masking of Inflammation and Fever

The pharmacological activity of NAPROXEN Tablets, EC-NAPROXEN, and NAPROXEN SODIUM in reducing inflammation, and possibly fever, may diminish the utility of diagnostic signs in detecting infections.

5.14 Long-Term Use and Laboratory Monitoring

Because serious GI bleeding, hepatotoxicity, and renal injury can occur without warning symptoms or signs, consider monitoring patients on long-term NSAID treatment with a CBC and a chemistry profile periodica ly [ see Warnings and Precautions (5.2, 5.3, 5.6) ].

Patients with initial hemoglobin values of 10g or less who are to receive long-term therapy should have hemoglobin values determined periodically.

Because of adverse eye findings in animal studies with drugs of this class, it is recommended that ophthalmic studies be carried out if any change or disturbance in vision occurs.

6 ADVERSE REACTIONS

The following adverse reactions are discussed in greater detail in other sections of the labeling:

- Cardiovascular Thrombotic Events [see Warnings and Precautions (5.1)]
- GI Bleeding, Ulceration and Perforation [see Warnings and Precautions (5.2)]
- Hepatotoxicity [see Warnings and Precautions (5.3)]
- Hypertension [see Warnings and Precautions (5.4)]
- Heart Failure and Edema [see Warnings and Precautions (5.5)]
- Renal Toxicity and Hyperkalemia [see Warnings and Precautions (5.6)]
- Anaphylactic Reactions [see Warnings and Precautions (5.7)]
- Serious Skin Reactions [see Warnings and Precautions (5.9)]
- Hematologic Toxicity [see Warnings and Precautions (5.12)]

6.1 Clinical Trials Experience

Because clinical trials are conducted under widely varying conditions, adverse reaction rates observed in the clinical trials of a drug cannot be directly compared to rates in the clinical trials of another drug and may not reflect the rates observed in practice.

Adverse reactions reported in controlled clinical trials in 960 patients treated for rheumatoid arthritis or osteoarthritis are listed below. In general, reactions in patients treated chronically were reported 2 to 10 times more frequently than they were in short-term studies in the 962 patients treated for mild to moderate pain or for dysmenorrhea. The most frequent complaints reported related to the gastrointestinal tract.

A clinical study found gastrointestinal reactions to be more frequent and more severe in rheumatoid arthritis patients taking daily doses of 1500 mg naproxen compared to those taking 750 mg naproxen.

In controlled clinical trials with about 80 pediatric patients and in well-monitored, open-label studies with about 400 pediatric patients with polyarticular juvenile idiopathic arthritis treated with naproxen, the incidence of rash and prolonged bleeding times were greater, the incidence of gastrointestinal and central nervous system reactions were about the same, and the incidence of other reactions were lower in pediatric patients than in adults.

In patients taking naproxen in clinical trials, the most frequently reported adverse experiences in approximately 1% to 10% of patients were:

Gastrointestinal (GI) Experiences, including:heartburn*, abdominal pain*, nausea*, constipation*, diarrhea, dyspepsia, stomatitis

Central Nervous System:headache*, dizziness*, drowsiness*, lightheadedness, vertigo

Dermatologic:pruritus (itching)*, skin eruptions*, ecchymoses*, sweating, purpura

Special Senses:tinnitus*, visual disturbances, hearing disturbances

Cardiovascular:edema*, palpitations

General:dyspnea*, thirst

*Incidence of reported reaction between 3% and 9%. Those reactions occurring in less than 3% of the patients are unmarked.

In patients taking NSAIDs, the following adverse experiences have also been reported in approximately 1% to 10% of patients.

Gastrointestinal (GI) Experiences, including:flatulence, gross bleeding/perforation, GI ulcers (gastric/duodenal), vomiting

General:abnormal renal function, anemia, elevated liver enzymes, increased bleeding time, rashes

The following are additional adverse experiences reported in <1% of patients taking naproxen during clinical trials.

Gastrointestinal:pancreatitis, vomiting

Hepatobiliary:jaundice

Hemic and Lymphatic:melena, thrombocytopenia, agranulocytosis

Nervous System:inability to concentrate

Dermatologic:skin rashes

6.2 Postmarketing Experience

The following adverse reactions have been identified during post approval use of naproxen. Because these reactions are reported voluntarily from a population of uncertain size, it is not always possible to reliably estimate their frequency or establish a causal relationship to drug exposure.

The following are additional adverse experiences reported in <1% of patients taking naproxen during clinical trials and through postmarketing reports. Those adverse reactions observed through postmarketing reports are italicized.

Body as a Whole:anaphylactoid reactions, angioneurotic edema, menstrual disorders, pyrexia (chills and fever)

Cardiovascular:congestive heart failure, vasculitis, hypertension, pulmonary edema

Gastrointestinal:inflammation, bleeding (sometimes fatal, particularly in the elderly), ulceration, perforation and obstruction of the upper or lower gastrointestinal tract. Esophagitis, stomatitis, hematemesis, colitis, exacerbation of inflammatory bowel disease (ulcerative colitis, Crohn's disease).

Hepatobiliary:abnormal liver function tests, hepatitis (some cases have been fatal)

Hemic and Lymphatic:eosinophilia, leucopenia, granulocytopenia, hemolytic anemia, aplastic anemia

Metabolic and Nutritional:hyperglycemia, hypoglycemia

Nervous System:depression, dream abnormalities, insomnia, malaise, myalgia, muscle weakness, aseptic meningitis, cognitive dysfunction, convulsions

Respiratory:eosinophilic pneumonitis, asthma

Dermatologic:alopecia, urticaria, toxic epidermal necrolysis, erythema multiforme, erythema nodosum, fixed drug eruption, lichen planus, pustular reaction, systemic lupus erythematoses, bullous reactions, including Stevens-Johnson syndrome, photosensitive dermatitis, photosensitivity reactions, including rare cases resembling porphyria cutanea tarda (pseudoporphyria) or epidermolysis bullosa. If skin fragility, blistering or other symptoms suggestive of pseudoporphyria occur, treatment should be discontinued and the patient monitored.

Special Senses:hearing impairment, corneal opacity, papillitis, retrobulbar optic neuritis, papilledema

Urogenital:glomerular nephritis, hematuria, hyperkalemia, interstitial nephritis, nephrotic syndrome, renal disease, renal failure, renal papillary necrosis, raised serum creatinine

Reproduction (female):infertility

In patients taking NSAIDs, the following adverse experiences have also been reported in <1% of patients.

Body as a Whole:fever, infection, sepsis, anaphylactic reactions, appetite changes, death

Cardiovascular:hypertension, tachycardia, syncope, arrhythmia, hypotension, myocardial infarction

Gastrointestinal:dry mouth, esophagitis, gastric/peptic ulcers, gastritis, glossitis, eructation

Hepatobiliary:hepatitis, liver failure

Hemic and Lymphatic:rectal bleeding, lymphadenopathy, pancytopenia

Metabolic and Nutritional:weight changes

Nervous System:anxiety, asthenia, confusion, nervousness, paresthesia, somnolence, tremors, convulsions, coma, hallucinations

Respiratory:asthma, respiratory depression, pneumonia

Dermatologic:exfoliative dermatitis

Special Senses:blurred vision, conjunctivitis

Urogenital:cystitis, dysuria, oliguria/polyuria, proteinuria

7 DRUG INTERACTIONS

See Table 1 for clinically significant drug interactions with naproxen.

Table 1: Clinically Significant Drug Interactions with naproxen

Drugs That Interfere with Hemostasis
Clinical Impact: | - Naproxen and anticoagulants such as warfarin have a synergistic effect on bleeding. The concomitant use of naproxen and anticoagulants have an increased risk of serious bleeding compared to the use of either drug alone. - Serotonin release by platelets plays an important role in hemostasis. Case-control and cohort epidemiological studies showed that concomitant use of drugs that interfere with serotonin reuptake and an NSAID may potentiate the risk of bleeding more than an NSAID alone.
Intervention: | - Monitor patients with concomitant use of NAPROXEN Tablets, EC-NAPROXEN, or NAPROXEN SODIUM with anticoagulants (e.g., warfarin), antiplatelet agents (e.g., aspirin), selective serotonin reuptake inhibitors (SSRIs), and serotonin norepinephrine reuptake inhibitors (SNRIs) for signs of bleeding [see Warnings and Precautions (5.12)] .
Aspirin
Clinical Impact: | A pharmacodynamic (PD) study has demonstrated an interaction in which lower dose naproxen (220mg/day or 220mg twice daily) interfered with the antiplatelet effect of low-dose immediate-release aspirin, with the interaction most marked during the washout period of naproxen [ see Clinical Pharmacology (12.2)]. There is reason to expect that the interaction would be present with prescription doses of naproxen or with enteric-coated low-dose aspirin; however, the peak interference with aspirin function may be later than observed in the PD study due to the longer washout period. Controlled clinical studies showed that the concomitant use of NSAIDs and analgesic doses of aspirin does not produce any greater therapeutic effect than the use of NSAIDs alone. In a clinical study, the concomitant use of an NSAID and aspirin was associated with a significantly increased incidence of GI adverse reactions as compared to use of the NSAID alone [see Warnings and Precautions (5.2)] .
Intervention: | Because there may be an increased risk of cardiovascular events following discontinuation of naproxen due to the interference with the antiplatelet effect of aspirin during the washout period, for patients taking low-dose aspirin for cardioprotection who require intermittent analgesics, consider use of an NSAID that does not interfere with the antiplatelet effect of aspirin, or non-NSAID analgesics where appropriate. Concomitant use of NAPROXEN Tablets, EC-NAPROXEN, or NAPROXEN SODIUM and analgesic doses of aspirin is not generally recommended because of the increased risk of bleeding [see Warnings and Precautions (5.12)].; NAPROXEN Tablets, EC-NAPROXEN, or NAPROXEN SODIUM are not substitute for low dose aspirin for cardiovascular protection.
ACE Inhibitors, Angiotensin Receptor Blockers, and Beta-Blockers
Clinical Impact: | - NSAIDs may diminish the antihypertensive effect of angiotensin converting enzyme (ACE) inhibitors, angiotensin receptor blockers (ARBs), or beta-blockers (including propranolol). - In patients who are elderly, volume-depleted (including those on diuretic therapy), or have renal impairment, co-administration of an NSAID with ACE inhibitors or ARBs may result in deterioration of renal function, including possible acute renal failure. These effects are usually reversible.
Intervention: | - During concomitant use of NAPROXEN Tablets, EC-NAPROXEN, or NAPROXEN SODIUM and ACE-inhibitors, ARBs, or beta-blockers, monitor blood pressure to ensure that the desired blood pressure is obtained. - During concomitant use of NAPROXEN Tablets, EC-NAPROXEN, or NAPROXEN SODIUM and ACE-inhibitors or ARBs in patients who are elderly, volume-depleted, or have impaired renal function, monitor for signs of worsening renal function [ see Warnings and Precautions (5.6)]. - When these drugs are administered concomitantly, patients should be adequately hydrated. Assess renal function at the beginning of the concomitant treatment and periodically thereafter.
Diuretics
Clinical Impact: | Clinical studies, as well as post-marketing observations, showed that NSAIDs reduced the natriuretic effect of loop diuretics (e.g., furosemide) and thiazide diuretics in some patients. This effect has been attributed to the NSAID inhibition of renal prostaglandin synthesis.
Intervention | During concomitant use of NAPROXEN Tablets, EC-NAPROXEN, or NAPROXEN SODIUM with diuretics, observe patients for signs of worsening renal function, in addition to assuring diuretic efficacy including antihypertensive effects [ see Warnings and Precautions (5.6)].
Digoxin
Clinical Impact: | The concomitant use of naproxen with digoxin has been reported to increase the serum concentration and prolong the half-life of digoxin.
Intervention: | During concomitant use of NAPROXEN Tablets, EC-NAPROXEN, or NAPROXEN SODIUM and digoxin, monitor serum digoxin levels.
Lithium
Clinical Impact: | NSAIDs have produced elevations in plasma lithium levels and reductions in renal lithium clearance. The mean minimum lithium concentration increased 15%, and the renal clearance decreased by approximately 20%. This effect has been attributed to NSAID inhibition of renal prostaglandin synthesis.
Intervention: | During concomitant use of NAPROXEN Tablets, EC-NAPROXEN, or NAPROXEN SODIUM and lithium, monitor patients for signs of lithium toxicity.
Methotrexate
Clinical Impact: | Concomitant use of NSAIDs and methotrexate may increase the risk for methotrexate toxicity (e.g., neutropenia, thrombocytopenia, renal dysfunction).
Intervention: | During concomitant use of NAPROXEN Tablets, EC-NAPROXEN, or NAPROXEN SODIUM and methotrexate, monitor patients for methotrexate toxicity.
Cyclosporine
Clinical Impact: | Concomitant use of NAPROXEN Tablets, EC-NAPROXEN, or NAPROXEN SODIUM and cyclosporine may increase cyclosporine's nephrotoxicity.
Intervention: | During concomitant use of NAPROXEN Tablets, EC-NAPROXEN, or NAPROXEN SODIUM and cyclosporine, monitor patients for signs of worsening renal function.
NSAIDs and Salicylates
Clinical Impact: | Concomitant use of naproxen with other NSAIDs or salicylates (e.g., diflunisal, salsalate) increases the risk of GI toxicity, with little or no increase in efficacy [ see Warnings and Precautions (5.2)].
Intervention: | The concomitant use of naproxen with other NSAIDs or salicylates is not recommended.
Pemetrexed
Clinical Impact: | Concomitant use of NAPROXEN Tablets, EC-NAPROXEN, or NAPROXEN SODIUM and pemetrexed may increase the risk of pemetrexed-associated myelosuppression, renal, and GI toxicity (see the pemetrexed prescribing information).
Intervention: | During concomitant use of NAPROXEN Tablets, EC-NAPROXEN, or NAPROXEN SODIUM and pemetrexed, in patients with renal impairment whose creatinine clearance ranges from 45 to 79 mL/min, monitor for myelosuppression, renal and GI toxicity.; NSAIDs with short elimination half-lives (e.g., diclofenac, indomethacin) should be avoided for a period of two days before, the day of, and two days following administration of pemetrexed.; In the absence of data regarding potential interaction between pemetrexed and NSAIDs with longer half-lives (e.g., meloxicam, nabumetone), patients taking these NSAIDs should interrupt dosing for at least five days before, the day of, and two days following pemetrexed administration.
Antacids and Sucralfate
Clinical Impact: | Concomitant administration of some antacids (magnesium oxide or aluminum hydroxide) and sucralfate can delay the absorption of naproxen.
Intervention: | Concomitant administration of antacids such as magnesium oxide or aluminum hydroxide, and sucralfate with NAPROXEN Tablets, EC-NAPROXEN, or NAPROXEN SODIUM is not recommended.
Cholestyramine
Clinical Impact: | Concomitant administration of cholestyramine can delay the absorption of NAPROXEN Tablets, EC-NAPROXEN, or NAPROXEN SODIUM.
Intervention: | Concomitant administration of cholestyramine with naproxen tablets is not recommended.
Probenecid
Clinical Impact: | Probenecid given concurrently increases naproxen anion plasma levels and extends its plasma half-life significantly.
Intervention: | Patients simultaneously receiving NAPROXEN Tablets, EC-NAPROXEN, or NAPROXEN SODIUM and probenecid should be observed for adjustment of dose if required.
Other albumin-bound drugs
Clinical Impact: | Naproxen is highly bound to plasma albumin; it thus has a theoretical potential for interaction with other albumin-bound drugs such as coumarin-type anticoagulants, sulphonylureas, hydantoins, other NSAIDs, and aspirin.
Intervention: | Patients simultaneously receiving NAPROXEN Tablets, EC-NAPROXEN, or NAPROXEN SODIUM and a hydantoin, sulphonamide or sulphonylurea should be observed for adjustment of dose if required.

Drug/Laboratory Test Interactions

Bleeding times
Clinical Impact: | Naproxen may decrease platelet aggregation and prolong bleeding time.
Intervention: | This effect should be kept in mind when bleeding times are determined.
Porter-Silber test
Clinical Impact: | The administration of naproxen may result in increased urinary values for 17ketogenic steroids because of an interaction between the drug and/or its metabolites with m-di-nitrobenzene used in this assay.
Intervention: | Although 17-hydroxy-corticosteroid measurements (Porter-Silber test) do not appear to be artifactually altered, it is suggested that therapy with naproxen be temporarily discontinued 72 hours before adrenal function tests are performed if the Porter-Silber test is to be used.
Urinary assays of 5-hydroxy indoleacetic acid (5HIAA)
Clinical Impact: | Naproxen may interfere with some urinary assays of 5-hydroxy indoleacetic acid (5HIAA).
Intervention: | This effect should be kept in mind when urinary 5-hydroxy indoleacetic acid is determined.

8 USE IN SPECIFIC POPULATIONS

8.1 Pregnancy

Risk Summary

Use of NSAIDs, including NAPROXEN Tablets, EC-NAPROXEN, and NAPROXEN SODIUM, can cause premature closure of the fetal ductus arteriosus and fetal renal dysfunction leading to oligohydramnios and, in some cases, neonatal renal impairment. Because of these risks, limit dose and duration of NAPROXEN Tablets, EC-NAPROXEN, or NAPROXEN SODIUM use between about 20 and 30 weeks of gestation, and avoid NAPROXEN Tablets, EC-NAPROXEN, and NAPROXEN SODIUM use at about 30 weeks of gestation and later in pregnancy [see Clinical Considerations, Data].

Premature Closure of Fetal Ductus Arteriosus:

Use of NSAIDs, including NAPROXEN Tablets, EC-NAPROXEN, and NAPROXEN SODIUM, at about 30 weeks gestation or later in pregnancy increases the risk of premature closure of the fetal ductus arteriosus.

Oligohydramnios/Neonatal Renal Impairment:

Use of NSAIDs at about 20 weeks gestation or later in pregnancy has been associated with cases of fetal renal dysfunction leading to oligohydramnios, and in some cases, neonatal renal impairment.

Data from observational studies regarding potential embryofetal risks of NSAID use in women in the first or second trimesters of pregnancy are inconclusive. In the general U.S. population, a l clinica ly recognized pregnancies, regardless of drug exposure, have a background rate of 2-4% for major malformations, and 15-20% for pregnancy loss. In animal reproduction studies in rats, rabbits, and mice no evidence of teratogenicity or fetal harm when naproxen was administered during the period of organogenesis at doses 0.13, 0.26, and 0.6 times the maximum recommended human daily dose of 1500 mg/day, respectively [see Data] . Based on animal data, prostaglandins have been shown to have an important role in endometrial vascular permeability, blastocyst implantation, and decidualization. In animal studies, administration of prostaglandin synthesis inhibitors such as naproxen, resulted in increased pre- and post-implantation loss. Prostaglandins also have been shown to have an important role in fetal kidney development. In published animal studies, prostaglandin synthesis inhibitors have been reported to impair kidney development when administered at clinically relevant doses.

The estimated background risk of major birth defects and miscarriage for the indicated population(s) is unknown. All pregnancies have a background risk of birth defect, loss, or other adverse outcomes. In the U.S. general population, the estimated background risk of major birth defects and miscarriage in clinically recognized pregnancies is 2% to 4% and 15% to 20%, respectively.

Clinical Considerations

Fetal/Neonatal Adverse Reactions

Premature Closure of Fetal Ductus Arteriosus:

Avoid use of NSAIDs in women at about 30 weeks gestation and later in pregnancy, because NSAIDs, including NAPROXEN Tablets, EC-NAPROXEN, and NAPROXEN SODIUM, can cause premature closure of the fetal ductus arteriosus [see Data].

Oligohydramnios/Neonatal Renal Impairment:

If an NSAID is necessary at about 20 weeks gestation or later in pregnancy, limit the use to the lowest effective dose and shortest duration possible. If NAPROXEN Tablets, EC-NAPROXEN, or NAPROXEN SODIUM treatment extends beyond 48 hours, consider monitoring with ultrasound for oligohydramnios. If oligohydramnios occurs, discontinue NAPROXEN Tablets, EC-NAPROXEN, and NAPROXEN SODIUM, and follow up according to clinical practice [see Data].

Labor or Delivery

There are no studies on the effects of NAPROXEN Tablets, EC-NAPROXEN, or NAPROXEN SODIUM during labor or delivery. In animal studies, NSAIDS, including naproxen, inhibit prostaglandin synthesis, cause delayed parturition, and increase the incidence of stillbirth.

Data

Human Data

There is some evidence to suggest that when inhibitors of prostaglandin synthesis are used to delay preterm labor, there is an increased risk of neonatal complications such as necrotizing enterocolitis, patent ductus arteriosus, and intracranial hemorrhage.

Naproxen treatment given in late pregnancy to delay parturition has been associated with persistent pulmonary hypertension, renal dysfunction, and abnormal prostaglandin E levels in preterm infants. Because of the known effects of nonsteroidal anti- inflammatory drugs on the fetal cardiovascular system (closure of ductus arteriosus), use during pregnancy (particularly starting at 30-weeks of gestation, or third trimester) should be avoided.

Premature Closure of Fetal Ductus Arteriosus

Published literature reports that the use of NSAIDs at about 30 weeks of gestation and later in pregnancy may cause premature closure of the fetal ductus arteriosus.

Oligohydramnios/Neonatal Renal Impairment:

Published studies and postmarketing reports describe maternal NSAID use at about 20 weeks gestation or later in pregnancy associated with fetal renal dysfunction leading to oligohydramnios, and in some cases, neonatal renal impairment. These adverse outcomes are seen, on average, after days to weeks of treatment,although oligohydramnios has been infrequently reported as soon as 48 hours after NSAID initiation. In many cases, but not all, the decrease in amniotic fluid was transient and reversible with cessation of the drug. There have been a limited number of case reports of maternal NSAID use and neonatal renal dysfunction without oligohydramnios, some of which were irreversible. Some cases of neonatal renal dysfunction required treatment with invasive procedures, such as exchange transfusion or dialysis.

Methodological limitations of these postmarketing studies and reports include lack of a control group; limited information regarding dose, duration, and timing of drug exposure; and concomitant use of other medications.These limitations preclude establishing a reliable estimate of the risk of adverse fetal and neonatal outcomes with maternal NSAID use. Because the published safety data on neonatal outcomes involved mostly preterm infants, the generalizability of certain reported risks to the full-term infant exposed to NSAIDs through maternal use is uncertain.

Animal data

Reproduction studies have been performed in rats at 20 mg/kg/day (0.13 times the maximum recommended human daily dose of 1500 mg/day based on body surface area comparison), rabbits at 20 mg/kg/day (0.26 times the maximum recommended human daily dose, based on body surface area comparison), and mice at 170 mg/kg/day (0.6 times the maximum recommended human daily dose based on body surface area comparison) with no evidence of impaired fertility or harm to the fetus due to the drug.

8.2 Lactation

Risk Summary

The naproxen anion has been found in the milk of lactating women at a concentration equivalent to approximately 1% of maximum naproxen concentration in plasma.
The developmental and health benefits of breastfeeding should be considered along with the mother's clinical need for NAPROXEN Tablets, EC-NAPROXEN, or NAPROXEN SODIUM and any potential adverse effects on the breastfed infant from the NAPROXEN Tablets, EC-NAPROXEN, or NAPROXEN SODIUM or from the underlying maternal condition.

8.3 Females and Males of Reproductive Potential

Infertility

Females

Based on the mechanism of action, the use of prostaglandin-mediated NSAIDs, including NAPROXEN Tablets, EC-NAPROXEN, and NAPROXEN SODIUM, may delay or prevent rupture of ovarian follicles, which has been associated with reversible infertility in some women. Published animal studies have shown that administration of prostaglandin synthesis inhibitors has the potential to disrupt prostaglandin-mediated follicular rupture required for ovulation. Small studies in women treated with NSAIDs have also shown a reversible delay in ovulation. Consider withdrawal of NSAIDs, including NAPROXEN Tablets, EC-NAPROXEN and NAPROXEN SODIUM, in women who have difficulties conceiving or who are undergoing investigation of infertility.

8.4 Pediatric Use

Safety and effectiveness in pediatric patients below the age of 2 years have not been established. Pediatric dosing recommendations for polyarticular juvenile idiopathic arthritis are based on well-controlled studies [ see Dosage and Administration (2)]. There are no adequate effectiveness or dose-response data for other pediatric conditions, but the experience in polyarticular juvenile idiopathic arthritis and other use experience have established that single doses of 2.5 to 5 mg/kg as naproxen suspension, with total daily dose not exceeding 15 mg/kg/day, are well tolerated in pediatric patients over 2 years of age.

8.5 Geriatric Use

The hepatic and renal tolerability of long-term naproxen administration was studied in two double-blind clinical trials involving 586 patients. Of the patients studied, 98 patients were age 65 and older and 10 of the 98 patients were age 75 and older. NAPROXEN was administered at doses of 375 mg twice daily or 750 mg twice daily for up to 6 months. Transient abnormalities of laboratory tests assessing hepatic and renal function were noted in some patients, although there were no differences noted in the occurrence of abnormal values among different age groups.

Elderly patients, compared to younger patients, are at greater risk for NSAID-associated serious cardiovascular, gastrointestinal, and/or renal adverse reactions. If the anticipated benefit for the elderly patient outweighs these potential risks, start dosing at the low end of the dosing range, and monitor patients for adverse effects [ see Warnings and Precautions (5.1, 5.2, 5.3, 5.6, 5.14)].

Studies indicate that although total plasma concentration of naproxen is unchanged, the unbound plasma fraction of naproxen is increased in the elderly. The clinical significance of this finding is unclear, although it is possible that the increase in free naproxen concentration could be associated with an increase in the rate of adverse events per a given dosage in some elderly patients. Caution is advised when high doses are required and some adjustment of dosage may be required in elderly patients. As with other drugs used in the elderly, it is prudent to use the lowest effective dose.

Experience indicates that geriatric patients may be particularly sensitive to certain adverse effects of nonsteroidal anti-inflammatory drugs. Elderly or debilitated patients seem to tolerate peptic ulceration or bleeding less well when these events do occur. Most spontaneous reports of fatal GI events are in the geriatric population [ see Warnings and Precautions (5.2)].

Naproxen is known to be substantially excreted by the kidney, and the risk of toxic reactions to this drug may be greater in patients with impaired renal function. Because elderly patients are more likely to have decreased renal function, care should be taken in dose selection, and it may be useful to monitor renal function [ see Clinical Pharmacology (12.3)]. Geriatric patients may be at a greater risk for the development of a form of renal toxicity precipitated by reduced prostaglandin formation during administration of nonsteroidal anti-inflammatory drugs [ see Warnings and Precautions (5.6)].

8.6 Hepatic Impairment

Caution is advised when high doses are required and some adjustment of dosage may be required in these patients. It is prudent to use the lowest effective dose [ see Clinical Pharmacology (12.3)].

8.7 Renal Impairment

Naproxen-containing products are not recommended for use in patients with moderate to severe and severe renal impairment (creatinine clearance <30 mL/min) [ see Warnings and Precautions (5.6), Clinical Pharmacology (12.3)].

10 OVERDOSAGE

Symptoms following acute NSAID overdosages have been typically limited to lethargy, drowsiness, nausea, vomiting, and epigastric pain, which have been generally reversible with supportive care. Gastrointestinal bleeding has occurred. Hypertension, acute renal failure, respiratory depression, and coma have occurred, but were rare [ see Warnings and Precautions (5.1, 5.2) ]. Because naproxen sodium may be rapidly absorbed, high and early blood levels should be anticipated. A few patients have experienced convulsions, but it is not clear whether or not these were drug-related. It is not known what dose of the drug would be life threatening. [see Warnings and Precautions (5.1, 5.2, 5.4, 5.6)].

Manage patients with symptomatic and supportive care following an NSAID overdosage. There are no specific antidotes. Consider emesis and/or activated charcoal (60 grams to 100 grams in adults, 1 gram to 2 grams per kg of body weight in pediatric patients) and/or osmotic cathartic in symptomatic patients seen within four hours of ingestion or in patients with a large overdosage (5 to 10 times the recommended dosage). Forced diuresis, alkalinization of urine, hemodialysis, or hemoperfusion may not be useful due to high protein binding.

For additional information about overdosage treatment contact a poison control center (1-800-222-1222).

11 DESCRIPTION

NAPROXEN (naproxen) tablets, EC-NAPROXEN (naproxen) delayed-release tablets and NAPROXEN SODIUM (naproxen sodium) tablets are nonsteroidal anti-inflammatory drugs available as follows: NAPROXEN tablets are available as yellow tablets containing 500 mg of naproxen for oral administration.

EC-NAPROXEN delayed-release tablets are available as enteric-coated white tablets containing 375 mg of naproxen or 500 mg of naproxen for oral administration.

NAPROXEN SODIUM tablets are available as dark blue tablets containing 550 mg of naproxen sodium for oral administration.

Naproxen is a propionic acid derivative related to the arylacetic acid group of nonsteroidal anti-inflammatory drugs. The chemical names for naproxen and naproxen sodium are (S)-6-methoxy-α-methyl-2-naphthaleneacetic acid and (S)-6-methoxy-α-methyl-2-naphthaleneacetic acid, sodium salt, respectively. Naproxen has a molecular weight of 230.26 and a molecular formula of C14H14O3. Naproxen sodium has a molecular weight of 252.23 and a molecular formula of C14H14NaO3. Naproxen and naproxen sodium have the following structures, respectively:

Naproxen is an odorless, white to off-white crystalline substance. It is lipid-soluble, practically insoluble in water at low pH and freely soluble in water at high pH. The octanol/water partition coefficient of naproxen at pH 7.4 is 1.6 to 1.8. Naproxen sodium is a white to creamy white, crystalline solid, freely soluble in water at neutral pH.

The inactive ingredients in NAPROXEN tablets include: croscarmellose sodium, iron oxides, povidone and magnesium stearate.

The inactive ingredients in EC-NAPROXEN delayed release tablets include: croscarmellose sodium, povidone and magnesium stearate. The enteric coating dispersion contains methacrylic acid copolymer, talc, triethyl citrate, sodium hydroxide and purified water. The imprinting on the tablets is black ink. The dissolution of this enteric-coated naproxen tablet is pH dependent with rapid dissolution above pH 6. There is no dissolution below pH 4.

The inactive ingredients in NAPROXEN SODIUM tablets include: magnesium stearate, microcrystalline cellulose, povidone and talc. The coating suspension may contain hydroxypropyl methylcellulose 2910, Opaspray K-1-4227, polyethylene glycol 8000 or Opadry YS-1-4216.

12 CLINICAL PHARMACOLOGY

12.1 Mechanism of Action

Naproxen has analgesic, anti-inflammatory, and antipyretic properties. NAPROXEN SODIUM (naproxen sodium) has been developed as a more rapidly absorbed formulation of naproxen for use as an analgesic.

The mechanism of action of naproxen, like that of other NSAIDs, is not completely understood but involves inhibition of cyclooxygenase (COX-1 and COX-2).

Naproxen is a potent inhibitor of prostaglandin synthesis in vitro. Naproxen concentrations reached during therapy have produced in vivoeffects. Prostaglandins sensitize afferent nerves and potentiate the action of bradykinin in inducing pain in animal models. Prostaglandins are mediators of inflammation. Because naproxen is an inhibitor of prostaglandin synthesis, its mode of action may be due to a decrease of prostaglandins in peripheral tissues.

12.2 Pharmacodynamics

In a healthy volunteer study, 10 days of concomitant administration of naproxen 220 mg once-daily with low-dose immediate-release aspirin (81 mg) showed an interaction with the antiplatelet activity of aspirin as measured by % serum thromboxane B2 inhibition at 24 hours following the day 10 dose [98.7% (aspirin alone) vs 93.1% (naproxen and aspirin)]. The interaction was observed even following discontinuation of naproxen on day 11 (while aspirin dose was continued) but normalized by day 13. In the same study, the interaction was greater when naproxen was administered 30 minutes prior to aspirin [98.7% vs 87.7%] and minimal when aspirin was administered 30 minutes prior to naproxen [98.7% vs 95.4%].

Following administration of naproxen 220 mg twice-daily with low-dose immediate-release aspirin (first naproxen dose given 30 minutes prior to aspirin), the interaction was minimal at 24 h following day 10 dose [98.7% vs 95.7%]. However, the interaction was more prominent after discontinuation of naproxen (washout) on day 11 [98.7% vs 84.3%] and did not normalize completely by day 13 [98.5% vs 90.7%]. [see Drug Interactions (7)] .

12.3 Pharmacokinetics

Naproxen and naproxen sodium is rapidly and completely absorbed from the gastrointestinal tract with an in vivobioavailability of 95%. The different dosage forms of NAPROXEN are bioequivalent in terms of extent of absorption (AUC) and peak concentration (Cmax); however, the products do differ in their pattern of absorption. These differences between naproxen products are related to both the chemical form of naproxen used and its formulation. Even with the observed differences in pattern of absorption, the elimination half-life of naproxen is unchanged across products ranging from 12 to 17 hours. Steady-state levels of naproxen are reached in 4 days to 5 days, and the degree of naproxen accumulation is consistent with this half-life. This suggests that the differences in pattern of release play only a negligible role in the attainment of steady-state plasma levels.

Absorption

NAPROXEN Tablets/NAPROXEN SODIUM:
After administration of NAPROXEN Tablets, peak plasma levels are attained in 2 to 4 hours. After oral administration of NAPROXEN SODIUM, peak plasma levels are attained in 1 to 2 hours. The difference in rates between the two products is due to the increased aqueous solubility of the sodium salt of naproxen used in NAPROXEN SODIUM.

EC-NAPROXEN:
EC-NAPROXEN is designed with a pH-sensitive coating to provide a barrier to disintegration in the acidic environment of the stomach and to lose integrity in the more neutral environment of the small intestine. The enteric polymer coating selected for EC-NAPROXEN dissolves above pH 6. When EC-NAPROXEN was given to fasted subjects, peak plasma levels were attained about 4 to 6 hours following the first dose (range: 2 to 12 hours). An in vivo study in man using radiolabeled EC-NAPROXEN tablets demonstrated that EC-NAPROXEN dissolves primarily in the small intestine rather than in the stomach, so the absorption of the drug is delayed until the stomach is emptied.

When EC-NAPROXEN and NAPROXEN were given to fasted subjects (n=24) in a crossover study following 1 week of dosing, differences in time to peak plasma levels (Tmax) were observed, but there were no differences in total absorption as measured by Cmaxand AUC:

 | EC-NAPROXEN* 500 mg bid | EC-NAPROXEN* 500 mg bid
Cmax(µg/mL) | 94.9 (18%) | 97.4 (13%)
Tmax(hours) | 4 (39%) | 1.9 (61%)
AUC0–12 hr(µg∙hr/mL) | 845 (20%) | 767 (15%)

*Mean value (coefficient of variation)

Antacid Effects
When EC-NAPROXEN was given as a single dose with antacid (54 mEq buffering capacity), the peak plasma levels of naproxen were unchanged, but the time to peak was reduced (mean Tmaxfasted 5.6 hours, mean Tmaxwith antacid 5 hours), although not significantly. [ see Drug Interactions (7)].

Food Effects
When EC-NAPROXEN was given as a single dose with food, peak plasma levels in most subjects were achieved in about 12 hours (range: 4 to 24 hours). Residence time in the small intestine until disintegration was independent of food intake. The presence of food prolonged the time the tablets remained in the stomach, time to first detectable serum naproxen levels, and time to maximal naproxen levels (Tmax), but did not affect peak naproxen levels (Cmax).

Distribution

Naproxen has a volume of distribution of 0.16 L/kg. At therapeutic levels naproxen is greater than 99% albumin-bound. At doses of naproxen greater than 500 mg/day there is less than proportional increase in plasma levels due to an increase in clearance caused by saturation of plasma protein binding at higher doses (average trough Css36.5, 49.2 and 56.4 mg/L with 500, 1,000 and 1,500 mg daily doses of naproxen, respectively). The naproxen anion has been found in the milk of lactating women at a concentration equivalent to approximately 1% of maximum naproxen concentration in plasma [see Use in Specific Populations (8.2)] .

Elimination

Metabolism

Naproxen is extensively metabolized in the liver to 6-0-desmethyl naproxen, and both parent and metabolites do not induce metabolizing enzymes. Both naproxen and 6-0-desmethyl naproxen are further metabolized to their respective acyl glucuronide conjugated metabolites.

Excretion

The clearance of naproxen is 0.13 mL/min/kg. Approximately 95% of the naproxen from any dose is excreted in the urine, primarily as naproxen (<1%), 6-0-desmethyl naproxen (<1%) or their conjugates (66% to 92%). The plasma half-life of the naproxen anion in humans ranges from 12 to 17 hours. The corresponding half-lives of both naproxen's metabolites and conjugates are shorter than 12 hours, and their rates of excretion have been found to coincide closely with the rate of naproxen clearance from the plasma. Small amounts, 3% or less of the administered dose, are excreted in the feces. In patients with renal failure metabolites may accumulate [ see Warnings and Precautions (5.6)].

Specific Populations

Pediatric:

In pediatric patients aged 5 to 16 years with arthritis, plasma naproxen levels following a 5 mg/kg single dose of naproxen suspension [ see Dosage and Administration (2)] were found to be similar to those found in normal adults following a 500 mg dose. The terminal half-life appears to be similar in pediatric and adult patients. Pharmacokinetic studies of naproxen were not performed in pediatric patients younger than 5 years of age. Pharmacokinetic parameters appear to be similar following administration of naproxen suspension or tablets in pediatric patients.

Geriatric:

Studies indicate that although total plasma concentration of naproxen is unchanged, the unbound plasma fraction of naproxen is increased in the elderly, although the unbound fraction is <1% of the total naproxen concentration. Unbound trough naproxen concentrations in elderly subjects have been reported to range from 0.12% to 0.19% of total naproxen concentration, compared with 0.05% to 0.075% in younger subjects.

Hepatic Impairment:

Naproxen pharmacokinetics have not been determined in subjects with hepatic insufficiency.

Chronic alcoholic liver disease and probably other diseases with decreased or abnormal plasma proteins (albumin) reduce the total plasma concentration of naproxen, but the plasma concentration of unbound naproxen is increased.

Renal Impairment:

Naproxen pharmacokinetics have not been determined in subjects with renal insufficiency. Given that naproxen, its metabolites and conjugates are primarily excreted by the kidney, the potential exists for naproxen metabolites to accumulate in the presence of renal insufficiency. Elimination of naproxen is decreased in patients with severe renal impairment.

Drug Interaction Studies

Aspirin:When NSAIDs were administered with aspirin, the protein binding of NSAIDs were reduced, although the clearance of free NSAID was not altered. The clinical significance of this interaction is not known. See Table 1 for clinically significant drug interactions of NSAIDs with aspirin [see Drug Interactions (7)].

13 NONCLINICAL TOXICOLOGY

13.1 Carcinogenesis, Mutagenesis, Impairment of Fertility

Carcinogenesis

A 2-year study was performed in rats to evaluate the carcinogenic potential of naproxen at rat doses of 8, 16, and 24 mg/kg/day (0.05, 0.1, and 0.16 times the maximum recommended human daily dose [MRHD] of 1500 mg/day based on a body surface area comparison). No evidence of tumorigenicity was found.

Mutagenesis

Naproxen tested positive in the in vivosister chromatid exchange assay for but was not mutagenic in the in vitrobacterial reverse mutation assay (Ames test).

Impairment of Fertility

Male rats were treated with 2, 5, 10, and 20 mg/kg naproxen by oral gavage for 60 days prior to mating and female rats were treated with the same doses for 14 days prior to mating and for the first 7 days of pregnancy. There were no adverse effects on fertility noted (up to 0.13 times the MRDH based on body surface area).

14 CLINICAL STUDIES

Naproxen has been studied in patients with rheumatoid arthritis, osteoarthritis, juvenile arthritis, ankylosing spondylitis, tendonitis and bursitis, and acute gout. Improvement in patients treated for rheumatoid arthritis was demonstrated by a reduction in joint swelling, a reduction in duration of morning stiffness, a reduction in disease activity as assessed by both the investigator and patient, and by increased mobility as demonstrated by a reduction in walking time. Generally, response to naproxen has not been found to be dependent on age, sex, severity or duration of rheumatoid arthritis.

In patients with osteoarthritis, the therapeutic action of naproxen has been shown by a reduction in joint pain or tenderness, an increase in range of motion in knee joints, increased mobility as demonstrated by a reduction in walking time, and improvement in capacity to perform activities of daily living impaired by the disease.

In a clinical trial comparing standard formulations of naproxen 375 mg twice a day (750 mg a day) vs 750 mg twice a day (1500 mg/day), 9 patients in the 750 mg group terminated prematurely because of adverse events. Nineteen patients in the 1500 mg group terminated prematurely because of adverse events. Most of these adverse events were gastrointestinal events.

In clinical studies in patients with rheumatoid arthritis, osteoarthritis, and polyarticular juvenile idiopathic arthritis, naproxen has been shown to be comparable to aspirin and indomethacin in controlling the aforementioned measures of disease activity, but the frequency and severity of the milder gastrointestinal adverse effects (nausea, dyspepsia, heartburn) and nervous system adverse effects (tinnitus, dizziness, lightheadedness) were less in naproxen-treated patients than in those treated with aspirin or indomethacin.

In patients with ankylosing spondylitis, naproxen has been shown to decrease night pain, morning stiffness and pain at rest. In double-blind studies the drug was shown to be as effective as aspirin, but with fewer side effects.

In patients with acute gout, a favorable response to naproxen was shown by significant clearing of inflammatory changes (eg, decrease in swelling, heat) within 24 to 48 hours, as well as by relief of pain and tenderness.

Naproxen has been studied in patients with mild to moderate pain secondary to postoperative, orthopedic, postpartum episiotomy and uterine contraction pain and dysmenorrhea. Onset of pain relief can begin within 1 hour in patients taking naproxen and within 30 minutes in patients taking naproxen sodium. Analgesic effect was shown by such measures as reduction of pain intensity scores, increase in pain relief scores, decrease in numbers of patients requiring additional analgesic medication, and delay in time to remedication. The analgesic effect has been found to last for up to 12 hours.

Naproxen may be used safely in combination with gold salts and/or corticosteroids; however, in controlled clinical trials, when added to the regimen of patients receiving corticosteroids, it did not appear to cause greater improvement over that seen with corticosteroids alone. Whether naproxen has a "steroid-sparing" effect has not been adequately studied. When added to the regimen of patients receiving gold salts, naproxen did result in greater improvement. Its use in combination with salicylates is not recommended because there is evidence that aspirin increases the rate of excretion of naproxen and data are inadequate to demonstrate that naproxen and aspirin produce greater improvement over that achieved with aspirin alone. In addition, as with other NSAIDs, the combination may result in higher frequency of adverse events than demonstrated for either product alone.

In^51Cr blood loss and gastroscopy studies with normal volunteers, daily administration of 1000 mg of NAPROXEN (naproxen) or 1100 mg of NAPROXEN SODIUM (naproxen sodium) has been demonstrated to cause statistically significantly less gastric bleeding and erosion than 3250 mg of aspirin.

Three 6-week, double-blind, multicenter studies with EC-NAPROXEN (naproxen) (375 or 500 mg twice a day, n=385) and NAPROXEN (375 or 500 mg bid, n=279) were conducted comparing EC-NAPROXEN with NAPROXEN, including 355 rheumatoid arthritis and osteoarthritis patients who had a recent history of NSAID-related GI symptoms. These studies indicated that EC-NAPROXEN and NAPROXEN showed no significant differences in efficacy or safety and had similar prevalence of minor GI complaints. Individual patients, however, may find one formulation preferable to the other.

Five hundred and fifty-three patients received EC-NAPROXEN during long-term open-label trials (mean length of treatment was 159 days). The rates for clinically-diagnosed peptic ulcers and GI bleeds were similar to what has been historically reported for long-term NSAID use.

16 HOW SUPPLIED/STORAGE AND HANDLING

EC-Naproxen (naproxen delayed-release tablets) 500 mg: white, oblong coated tablets imprinted with NPR EC 500 on one side. Packaged in light-resistant bottles of 100. Supplied as:

NDC 72162-1935-1 100’s (bottle)

Store at 15°C to 30°C (59°F to 86°F) in well-closed containers; dispense in light-resistant containers.

Repackaged/Relabeled by:
Bryant Ranch Prepack, Inc.
Burbank, CA 91504

17 PATIENT COUNSELING INFORMATION

Advise the patient to read the FDA-approved patient labeling (Medication Guide) that accompanies each prescription dispensed. Inform patients, families, or their caregivers of the following information before initiating therapy with NAPROXEN Tablets, EC-NAPROXEN or NAPROXEN SODIUM and periodically during the course of ongoing therapy.

Cardiovascular Thrombotic Events

Advise patients to be alert for the symptoms of cardiovascular thrombotic events, including chest pain, shortness of breath, weakness, or slurring of speech, and to report any of these symptoms to their health care provider immediately [see Warnings and Precautions (5.1)] .

Gastrointestinal Bleeding, Ulceration, and Perforation

Advise patients to report symptoms of ulcerations and bleeding, including epigastric pain, dyspepsia, melena, and hematemesis to their health care provider. In the setting of concomitant use of low-dose aspirin for cardiac prophylaxis, inform patients of the increased risk for the signs and symptoms of GI bleeding [see Warnings and Precautions (5.2)] .

Hepatotoxicity

Inform patients of the warning signs and symptoms of hepatotoxicity (e.g., nausea, fatigue, lethargy, pruritus, diarrhea, jaundice, right upper quadrant tenderness, and "flu-like" symptoms). If these occur, instruct patients to stop NAPROXEN Tablets, EC-NAPROXEN or NAPROXEN SODIUM and seek immediate medical therapy [see Warnings and Precautions (5.3)] .

Heart Failure and Edema

Advise patients to be alert for the symptoms of congestive heart failure including shortness of breath, unexplained weight gain, or edema and to contact their healthcare provider if such symptoms occur [see Warnings and Precautions (5.5)] .

Anaphylactic Reactions

Inform patients of the signs of an anaphylactic reaction (e.g., difficulty breathing, swelling of the face or throat). Instruct patients to seek immediate emergency help if these occur [see Contraindications (4)and Warnings and Precautions (5.7)] .

Serious Skin Reactions,including DRESS

Advise patients to stop taking NAPROXEN Tablets, EC-NAPROXEN or NAPROXEN SODIUM immediately if they develop any type of rash or fever and to contact their healthcare provider as soon as possible [see Warnings and Precautions (5.9, 5.10)] .

Female Fertility

Advise females of reproductive potential who desire pregnancy that NSAIDs, including NAPROXEN Tablets, EC-NAPROXEN or NAPROXEN SODIUM, may be associated with a reversible delay in ovulation [see Use in Specific Populations (8.3)].

Fetal Toxicity

Inform pregnant women to avoid use of NAPROXEN Tablets, EC-NAPROXEN or NAPROXEN SODIUM and other NSAIDs starting at 30 weeks gestation because of the risk of the premature closing of the fetal ductus arteriosus. If treatment with NAPROXEN Tablets, EC-NAPROXEN, or NAPROXEN SODIUM is needed for a pregnant woman between about 20 to 30 weeks gestation, advise her that she may need to be monitored for oligohydramnios, if treatment continues for longer than 48 hours [see Warnings and Precautions (5.11)and Use in Specific Populations (8.1)].

Avoid Concomitant Use of NSAIDs

Inform patients that the concomitant use of NAPROXEN Tablets, EC-NAPROXEN or NAPROXEN SODIUM with other NSAIDs or salicylates (e.g., diflunisal, salsalate) is not recommended due to the increased risk of gastrointestinal toxicity, and little or no increase in efficacy [see Warnings and Precautions (5.2)and Drug Interactions (7)] . Alert patients that NSAIDs may be present in "over the counter" medications for treatment of colds, fever, or insomnia.

Use of NSAIDS and Low-Dose Aspirin

Inform patients not to use low-dose aspirin concomitantly with NAPROXEN Tablets, EC-NAPROXEN or NAPROXEN SODIUM until they talk to their healthcare provider [see Drug Interactions (7)] .

Manufactured for:
Atnahs Pharma US Limited, Miles Gray Road, Basildon, Essex, SS14 3FR, United Kingdom

Distributed by:
Woodward Pharma Services LLC, Wixom, MI 48393, United States

Medication Guide for Nonsteroidal Anti-Inflammatory Drugs (NSAIDs)

What is the most important information I should know about medicines called Non-Steroidal Anti- Inflammatory Drugs (NSAIDs)?

NSAIDs can cause serious side effects, including:

- Increased risk of a heart attack or stroke that can lead to death.This risk may happen early in treatment and may increase:
  - with increasing doses of NSAIDs
  - with longer use of NSAIDs

Do not take NSAIDs right before or after a heart surgery called a "coronary artery bypass graft (CABG)." Avoid taking NSAIDs after a recent heart attack, unless your healthcare provider tells you to. You may have an increased risk of another heart attack if you take NSAIDs after a recent heart attack.

- Increased risk of bleeding, ulcers, and tears (perforation) of the esophagus (tube leading from the mouth to the stomach), stomach and intestines:
  - any time during use
  - without warning symptoms
  - that may cause death

The risk of getting an ulcer or bleeding increases with:

- past history of stomach ulcers, or stomach or intestinal bleeding with use of NSAIDs
- taking medicines called "corticosteroids", "anticoagulants", "SSRIs", or "SNRIs"
- increasing doses of NSAIDs
- longer use of NSAIDs
- smoking
- drinking alcohol
- older age
- poor health
- advanced liver disease
- bleeding problems

NSAIDs should only be used:

- exactly as prescribed
- at the lowest dose possible for your treatment
- for the shortest time needed

What are NSAIDs?

NSAIDs are used to treat pain and redness, swelling, and heat (inflammation) from medical conditions such as different types of arthritis, menstrual cramps, and other types of short-term pain.

Who should not take NSAIDs?

Do not take NSAIDs:

- if you have had an asthma attack, hives, or other allergic reaction with aspirin or any other NSAIDs.
- right before or after heart bypass surgery.

Before taking NSAIDs, tell your healthcare provider about all of your medical conditions, including if you:

- have liver or kidney problems
- have high blood pressure
- have asthma
- are pregnant or plan to become pregnant. Talk to your healthcare provider if you are considering taking NSAIDs during pregnancy. You should not take NSAIDs after 29 weeks of pregnancy.
- are breastfeeding or plan to breastfeed .

Tell your healthcare provider about all of the medicines you take, including prescription or over-the-counter medicines, vitamins or herbal supplements.NSAIDs and some other medicines can interact with each other and cause serious side effects. Do not start taking any new medicine without talking to your healthcare provider first.

What are the possible side effects of NSAIDs?

NSAIDs can cause serious side effects, including:

See "What is the most important information I should know about medicines called Nonsteroidal Anti-inflammatory Drugs (NSAIDs)?

- new or worse high blood pressure
- heart failure
- liver problems including liver failure
- kidney problems including kidney failure
- low red blood cells (anemia)
- life-threatening skin reactions
- life-threatening allergic reactions
- Other side effects of NSAIDs include:stomach pain, constipation, diarrhea, gas, heartburn, nausea, vomiting, and dizziness.

Get emergency help right away if you have any of the following symptoms:

- shortness of breath or trouble breathing
- chest pain
- weakness in one part or side of your body
- slurred speech
- swelling of the face or throat

Stop taking your NSAID and call your healthcare provider right away if you get any of the following symptoms:

- nausea
- more tired or weaker than usual
- diarrhea
- itching
- your skin or eyes look yellow
- indigestion or stomach pain
- flu-like symptoms
- vomit blood
- there is blood in your bowel movement or it is black and sticky like tar
- unusual weight gain
- skin rash or blisters with fever
- swelling of the arms, legs, hands and feet

If you take too much of your NSAID, call your healthcare provider or get medical help right away.

These are not all the possible side effects of NSAIDs. For more information, ask your healthcare provider or pharmacist about NSAIDs.

Call your doctor for medical advice about side effects. You may report side effects to FDA at 1-800-FDA-1088.

Other information about NSAIDs

- Aspirin is an NSAID medicine but it does not increase the chance of a heart attack. Aspirin can cause bleeding in the brain, stomach, and intestines. Aspirin can also cause ulcers in the stomach and intestines.
- Some NSAIDs are sold in lower doses without a prescription (over-the-counter). Talk to your healthcare provider before using over-the-counter NSAIDs for more than 10 days.

General information about the safe and effective use of NSAIDs

Medicines are sometimes prescribed for purposes other than those listed in a Medication Guide. Do not use NSAIDs for a condition for which it was not prescribed. Do not give NSAIDs to other people, even if they have the same symptoms that you have. It may harm them.

If you would like more information about NSAIDs, talk with your healthcare provider. You can ask your pharmacist or healthcare provider for information about NSAIDs that is written for health professionals.

Manufactured for:Atnahs Pharma US Limited, Miles Gray Road, Basildon, Essex, SS14 3FR, United Kingdom

Distributed by:Woodward Pharma Services LLC, Wixom, MI 48393, United States
For more information, call 1-888-514-4727.

This Medication Guide has been approved by the U.S. Food and Drug Administration.
Issued or Revised: April 2021

PACKAGE LABEL

Naproxen DR 500 mg Tablet, #100